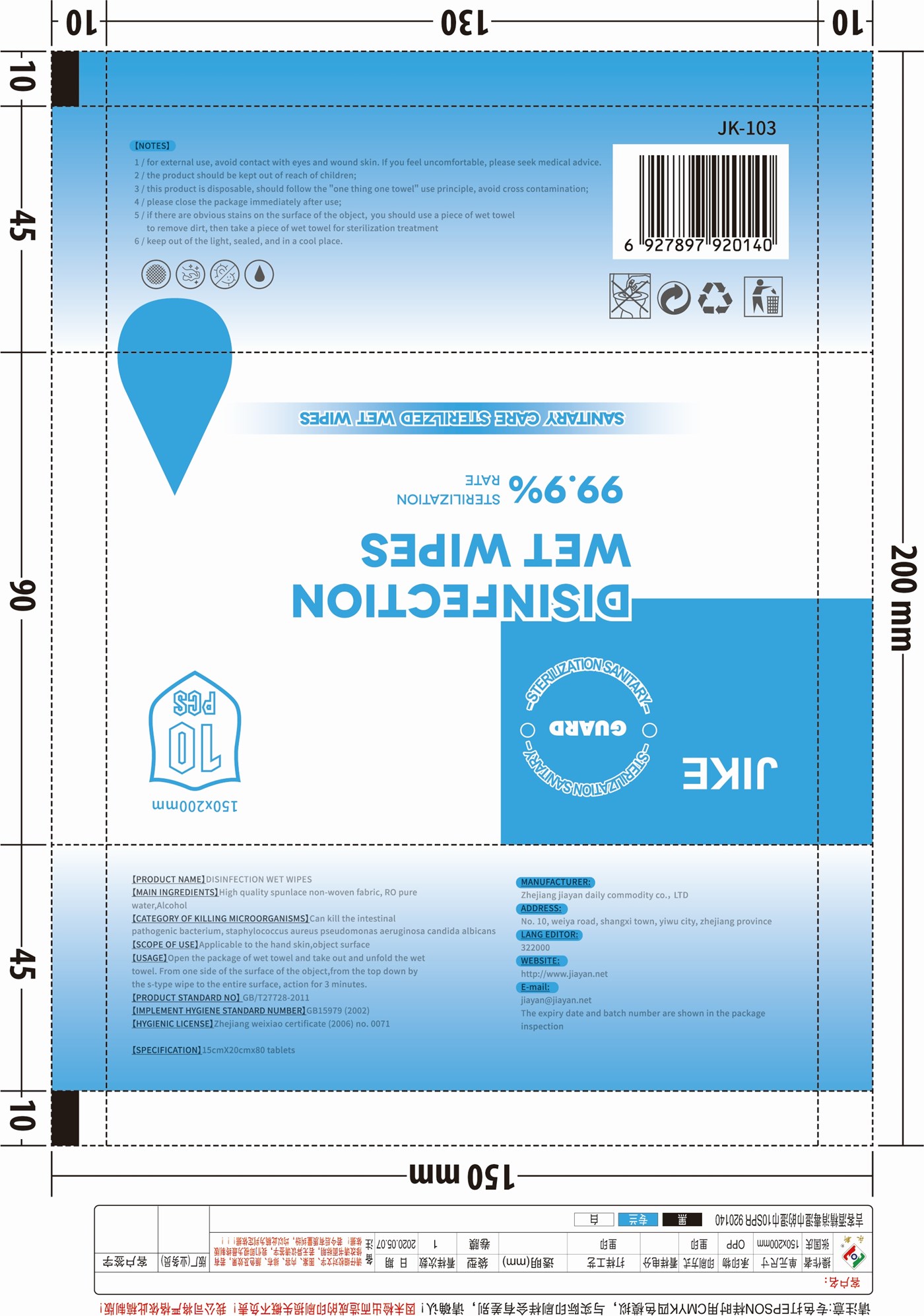 DRUG LABEL: sanitizing wipes
NDC: 42003-015 | Form: CLOTH
Manufacturer: Zhejiang jiayan daily commodity Co.,ltd
Category: otc | Type: HUMAN OTC DRUG LABEL
Date: 20200826

ACTIVE INGREDIENTS: ALCOHOL 0.75 mL/1 g
INACTIVE INGREDIENTS: WATER

sanitizing wipes

Active Ingredient(s)

75% ALCOHOL Purpose: Antiseptic

Purpose

Antiseptic

USE

Applicable to the hand skin, object surface

Warning

for external use, avoid contact with eyes and wound skin. If you feel uncomfortable, please seek medical advice.

the product should be kept out of reach of children.

this product is disposable, should follow the "one thing one towel" use principle, avoid contamination.

please close the package immediately after use

if there are obvious stains on the surface of the object, you should use a piece of wet towel to remove dirt, then take a piece of wet towel for sterilization treatment

keep out of the light, sealed and in a cool place

DO NOT USE

avoid contact with eyes and wound skin.

WHEN USING

If you feel uncomfortable, please seek medical advice.

KEEP OUT OF REACH OF CHILDREN

the product should be kept out of reach of children.

USAGE

Open the package of wet towel and take out and unfold the wet towel. From one side of the surface of the object, from the top down by the s-type wipe to the entire surface, action for 3 minutes.

Other information

this product is disposable, should follow the "one thing one towel" use principle, avoid contamination.

please close the package immediately after use

if there are obvious stains on the surface of the object, you should use a piece of wet towel to remove dirt, then take a piece of wet towel for sterilization treatment

keep out of the light, sealed and in a cool place

Inactive ingredients

RO pure WATER

Package Label - Principal Display Panel

10 PCS NDC: 42003-015-01

JIKE

150X200MM

10

PCS

STERILIZATION SANITARY

GUARD

DISINFECTION

WET WIPES

99.9% STERIZATION RATE

SANITARY CARE STERILZED WET WIPES